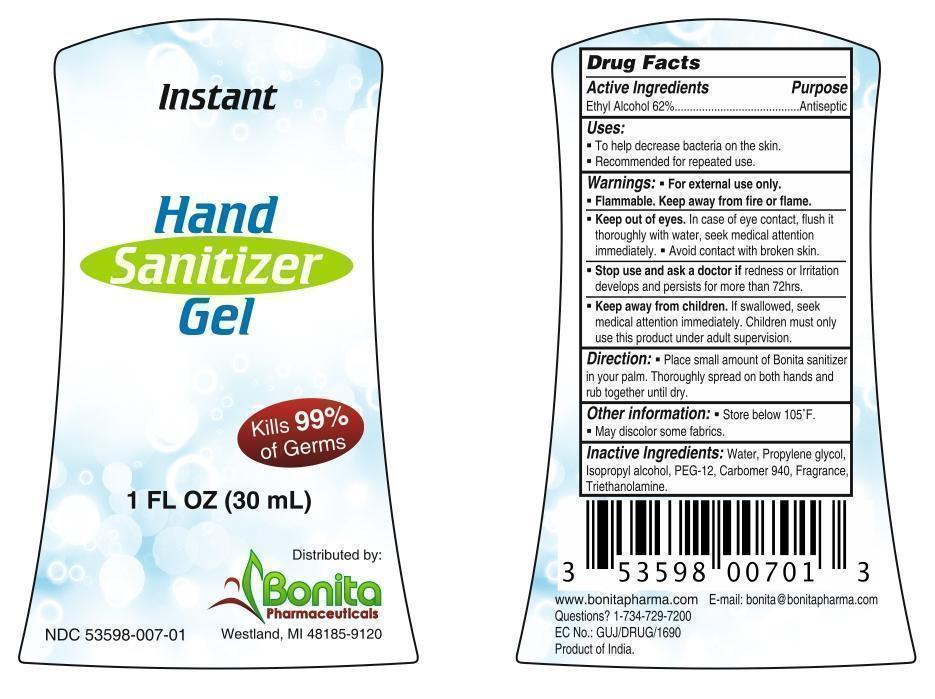 DRUG LABEL: Instant Hand Sanitizer Gel
NDC: 53598-007 | Form: GEL
Manufacturer: Bonita Pharmaceuticals LLC
Category: otc | Type: HUMAN OTC DRUG LABEL
Date: 20130912

ACTIVE INGREDIENTS: ALCOHOL 18.6 mL/30 mL
INACTIVE INGREDIENTS: WATER; PROPYLENE GLYCOL; ISOPROPYL ALCOHOL; POLYETHYLENE GLYCOL 600; CARBOMER 940; TROLAMINE

Instant Hand Sanitizer Gel

Drug Facts

Active Ingredients

Ethyl Alcohol 62%

Purpose

Antiseptic

Uses

- To help decrease bacteria on the skin.
- Recommended for repeated use.

Warnings

For external use only. Flammable, keep away from fire or flame.

DO NOT USE

- Keep out of eyes. In case of eye contact, flush it thoroughly with water, seek medical attention immediately.
- Avoid contact with broken skin.

- Stop use and ask a doctor if redness or Irritation develops and persists for more than 72hrs.

KEEP OUT OF REACH OF CHILDREN

- Keep away from children. If swallowed, seek medical attention immediately. Children must only use this product under adult supervision.

Direction

- Place small amount of Bonita sanitizer in your palm. Thoroughly spread on both hands and rub together until dry.

Other Information

- Store below 105 ˚F.
- May discolor some fabrics.

Inactive Ingredients

- Water
- Propylene glycol
- Isopropyl alcohol
- PEG-12
- Carbomer 940
- Fragrance
- Triethanolamine